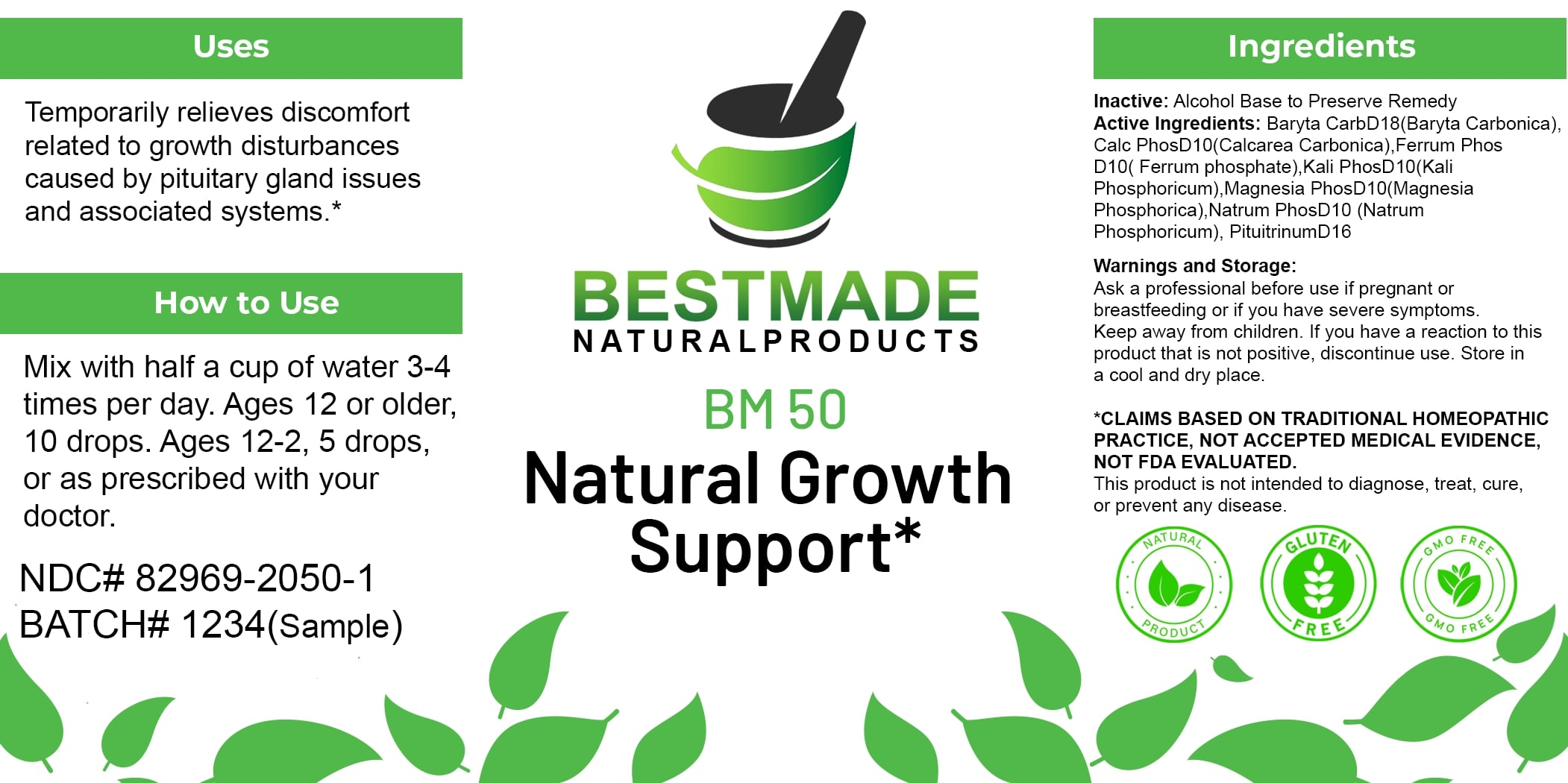 DRUG LABEL: Bestmade Natural Products BM50
NDC: 82969-2050 | Form: LIQUID
Manufacturer: Bestmade Natural Products
Category: homeopathic | Type: HUMAN OTC DRUG LABEL
Date: 20250123

ACTIVE INGREDIENTS: DIBASIC POTASSIUM PHOSPHATE 30 [hp_C]/30 [hp_C]; BOS TAURUS PITUITARY GLAND, POSTERIOR 30 [hp_C]/30 [hp_C]; BARIUM CARBONATE 30 [hp_C]/30 [hp_C]; FERROSOFERRIC PHOSPHATE 30 [hp_C]/30 [hp_C]; OYSTER SHELL CALCIUM CARBONATE, CRUDE 30 [hp_C]/30 [hp_C]; MAGNESIUM PHOSPHATE, DIBASIC TRIHYDRATE 30 [hp_C]/30 [hp_C]; SODIUM PHOSPHATE, DIBASIC, HEPTAHYDRATE 30 [hp_C]/30 [hp_C]
INACTIVE INGREDIENTS: ALCOHOL 30 [hp_C]/30 [hp_C]

BM50

DOSAGE AND ADMINISTRATION

How to Use

Mix with half a cup of water 3-4 times per day. Ages 12 or older, 10 drops. Ages 12-2, 5 drops, or as prescribed with your doctor.

INACTIVE INGREDIENT

Ingredients

Inactive: Alcohol Base to Preserve Remedy

ACTIVE INGREDIENT

Active Ingredients: Baryta Carb D18 (Baryta Carbonica), Calc Phos D10 (Calcarea Carbonica), Ferrum Phos D10 (Ferrum phosphate), Kali Phos D10 (Kali Phosphoricum), Magnesia Phos D10 (Magnesia Phosphorica), Natrum Phos D10 (Natrum Phosphoricum), Pituitrinum D16

Uses

Temporarily relieves discomfort related to growth disturbances caused by pituitary gland issues and associated systems.*

*CLAIMS BASED ON TRADITIONAL HOMEOPATHIC PRACTICE, NOT ACCEPTED MEDICAL EVIDENCE, NOT FDA EVALUATED.

This product is not intended to diagnose, treat, cure, or prevent any disease.

Uses

Temporarily relieves discomfort related to growth disturbances caused by pituitary gland issues and associated systems.*

*CLAIMS BASED ON TRADITIONAL HOMEOPATHIC PRACTICE, NOT ACCEPTED MEDICAL EVIDENCE, NOT FDA EVALUATED.

This product is not intended to diagnose, treat, cure, or prevent any disease.

KEEP OUT OF REACH OF CHILDREN

Warnings and Storage:

Ask a professional before use if pregnant or breastfeeding or if you have severe symptoms. Keep away from children. If you have a reaction to this product that is not positive, discontinue use. Store in a cool and dry place.

Warnings and Storage:

Ask a professional before use if pregnant or breastfeeding or if you have severe symptoms. Keep away from children. If you have a reaction to this product that is not positive, discontinue use. Store in a cool and dry place.

*CLAIMS BASED ON TRADITIONAL HOMEOPATHIC PRACTICE, NOT ACCEPTED MEDICAL EVIDENCE, NOT FDA EVALUATED.

This product is not intended to diagnose, treat, cure, or prevent any disease.

Entire package label